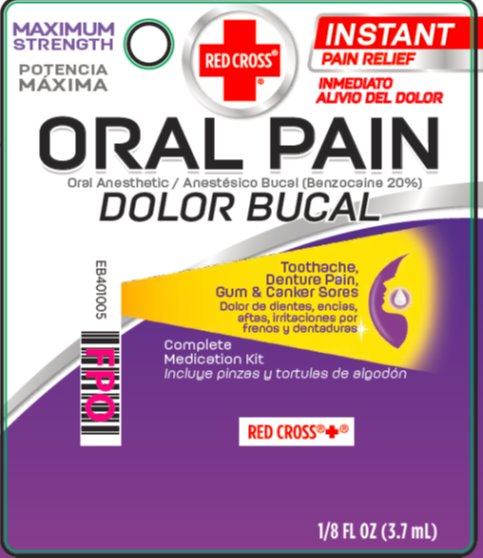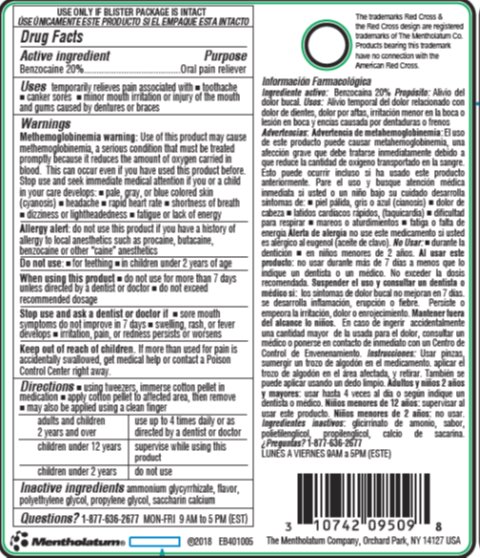 DRUG LABEL: Red Cross Oral Pain Relief
NDC: 10742-8902 | Form: LIQUID
Manufacturer: The Mentholatum Company
Category: otc | Type: HUMAN OTC DRUG LABEL
Date: 20241217

ACTIVE INGREDIENTS: BENZOCAINE 200 mg/1 mL
INACTIVE INGREDIENTS: AMMONIUM GLYCYRRHIZATE; POLYETHYLENE GLYCOL 400; PROPYLENE GLYCOL; SACCHARIN CALCIUM

Drug Facts - Red Cross Oral Pain Relief

Active ingredient

Benzocaine 20%

Purpose

Oral pain reliever

Uses

temporarily relieves pain associated with ▪ toothache ▪ canker sores ▪ minor mouth irritation or injury of the mouth and gums caused by dentures or braces

Warnings

Methemoglobinemia warning: Use of this product may cause methemoglobinemia, a serious condition that must be treated promptly because it reduces the amount of oxygen carried in blood. This can occur even if you have used this product before. Stop use and seek immediate medical attention if you or a child in your care develops: ▪ pale, gray, or blue colored skin (cyanosis) ▪ headache ▪ rapid heart rate ▪ shortness of breath ▪ dizziness or lightheadedness ▪ fatigue or lack of energy

Allergy alert: do not use this product if you have a history of allergy to local anesthetics such as procaine, butacaine, benzocaine or other “caine” anesthetics

Do Not Use

- for teething
- in children under 2 years of age

When using this product

- do not use for more than 7 days unless directed by a dentist or doctor
- do not exceed recommended dosage

Stop use and ask a doctor if

- sore mouth symptoms do not improve in 7 days
- swelling, rash, or fever develops
- irritation, pain, or redness persists or worsens

Keep Out of Reach of Children

If more than used for pain is accidentally swallowed, get medical help or contact a Poison Control Center right away.

Directions

- using tweezers, immerse cotton pellet in medication
- apply pellet to affected area, then remove
- adults and children 2 years and over: use up to 4 times daily or as directed by a dentist or doctor
- children under 12 years: supervise while using this product
- children under 2 years: do not use

Inactive Ingredients

ammonium glycyrrhizate, flavor, polyethylene glycol, propylene glycol, saccharin calcium